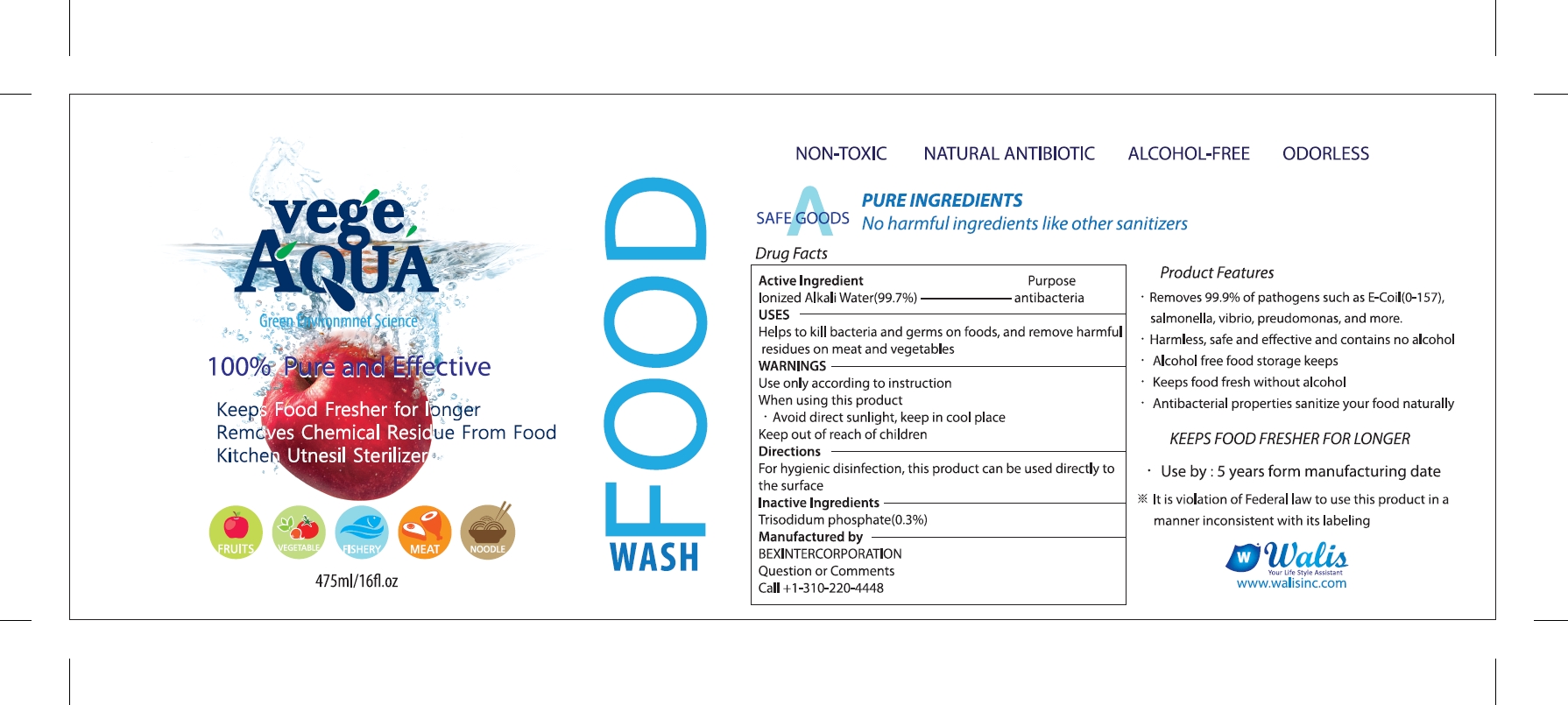 DRUG LABEL: VEGE AQUA
NDC: 70610-106 | Form: LIQUID
Manufacturer: KOTUKU INC.
Category: otc | Type: HUMAN OTC DRUG LABEL
Date: 20180905

ACTIVE INGREDIENTS: WATER 473.6 g/475 mL
INACTIVE INGREDIENTS: SODIUM PHOSPHATE, TRIBASIC, ANHYDROUS

VEGE AQUA